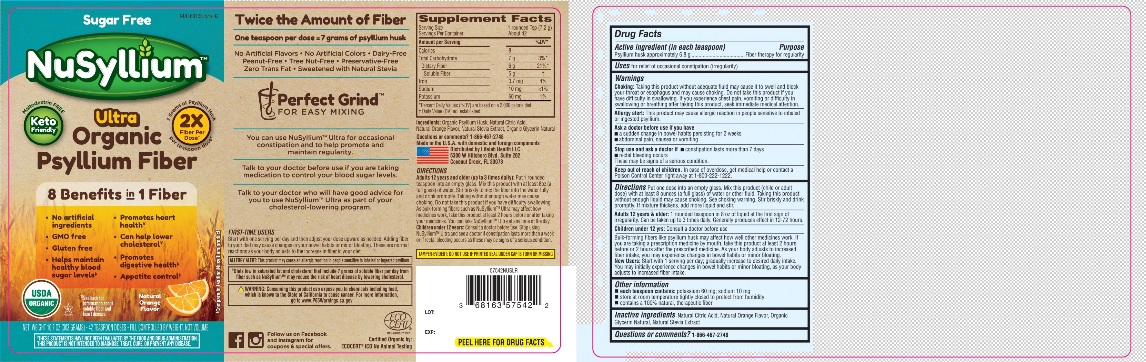 DRUG LABEL: Ultra Organic Fiber
NDC: 68163-575 | Form: POWDER
Manufacturer: Raritan Pharmaceuticals Inc
Category: otc | Type: HUMAN OTC DRUG LABEL
Date: 20250130

ACTIVE INGREDIENTS: PSYLLIUM HUSK 3.4 g/7 g
INACTIVE INGREDIENTS: ANHYDROUS CITRIC ACID; STEVIA REBAUDIANA LEAF; GLYCERIN

Active ingredient

Psyllium husk 3.4g (per each rounded teaspoon = 7g)

Purpose

Bulk-forming laxative

Use

effective in treating occasional constipation and restoring regularity

Warnings

Allergy alert: This product may cause an allergic reaction in people sensitive to inhaled or ingested psyllium.

Safety Warning

DO NOT USE IF PRINTED SEAL UNDER CAP IS TORN OR MISSING

Directions

Adults 12 Years and older (up to 3 times daily): Put 1 rounded TEASPOON into an empty glass. Mix this product with at least 8 oz (a full glass) of water.

Stir briskly to mix the fiber into the water fully and drink promptly. Taking without enough water may cause choking. Do not take this product if you have difficulty following.

As bulk-forming fibers such as NuSyllium Ultra may affect how medicines work, take this product at least 2 hours before or after taking your medicine,

You can take NuSyllium Ultra at any time of the day. Children under 12 years: Consult a doctor before use.

Stop using a NuSyllium and see a doctor if constipation lasts more than a week or if rectal bleeding occurs as these may be signs of a serious condition.

FIRST-TIME USERS

Start with one serving per day and then adjust your dose upwards as needed. Adding fiber to your diet may cause changes in your bowel habits or minor bloating.

These are normal reactions as your body adjusts to the increase fiber in your diet.

Other information

Diets low in saturated fat and cholesterol that include 7 grams of soluble fiber per day from fiber such as NuSyllium may reduce the risk of heart disease by lowering cholesterol.

These statements have not been evaluated by the Food and Drug Administration. This product is not intended to diagnose, treat, cure or prevent any disease.

Questions or comments?

1-866-467-2748

Inactive ingredients

Natural Citric Acid, Natural Flavors, Natural Stevia Extract, Organic Glycerin.

Principal Display Panel

NDC 68163-575-42

NuSyllium

Ultra Sugar Free Organic Fiber

7 GRAMS OF FIBER PER TEASPOON DOSE

Perfect Grind™ For Easy Mixing

- Fiber laxative for regularity
- Natural Orange Flavor

NO ARTIFICIAL INGREDIENTS

42 DOSES WEIGHT 10.7 OZ (300 GRAMS)

Fill controlled by weight, not volume

*Compared to leading NuSyllium product

Folks are Taking about the Benefits of NuSyllium Ultra Organic Natural Fiber!

- You can use NuSyllium Ultra to feel less hungry between meals.
- Maintain healthy blood sugar levels by using NuSyllium Ultra as part of your sugar free diet*. Talk to your doctor before use if you are taking medication to control your blood sugar levels.
- Organic NuSyllium is a great choice for promoting and maintain digestive health. You can use NuSyllium Ultra for occasional constipation and to help promote and maintain regularity.
- Did you know that one dose of NuSyllium Ultra contains 5 gm of soluble fiber? You can use it for lowering cholesterol and promoting heart health*.
- Talk to your doctor who will have good advice for you to use NuSyllium Ultra as part of your cholesterol –lowering program.

No Artificial Flavors, Peanut-free

No Artificial Colors, Tea Nut-free

GMO-free, Preservative-free

Gluten-free, Zero Trans Fat

Diary-free, No animal testing

Made in the U.S.A. with domestic and foreign components.

Distributed by: Lifelab Health LLC

6574 N.State Road #7 361

Coconut Creek, FL 33073